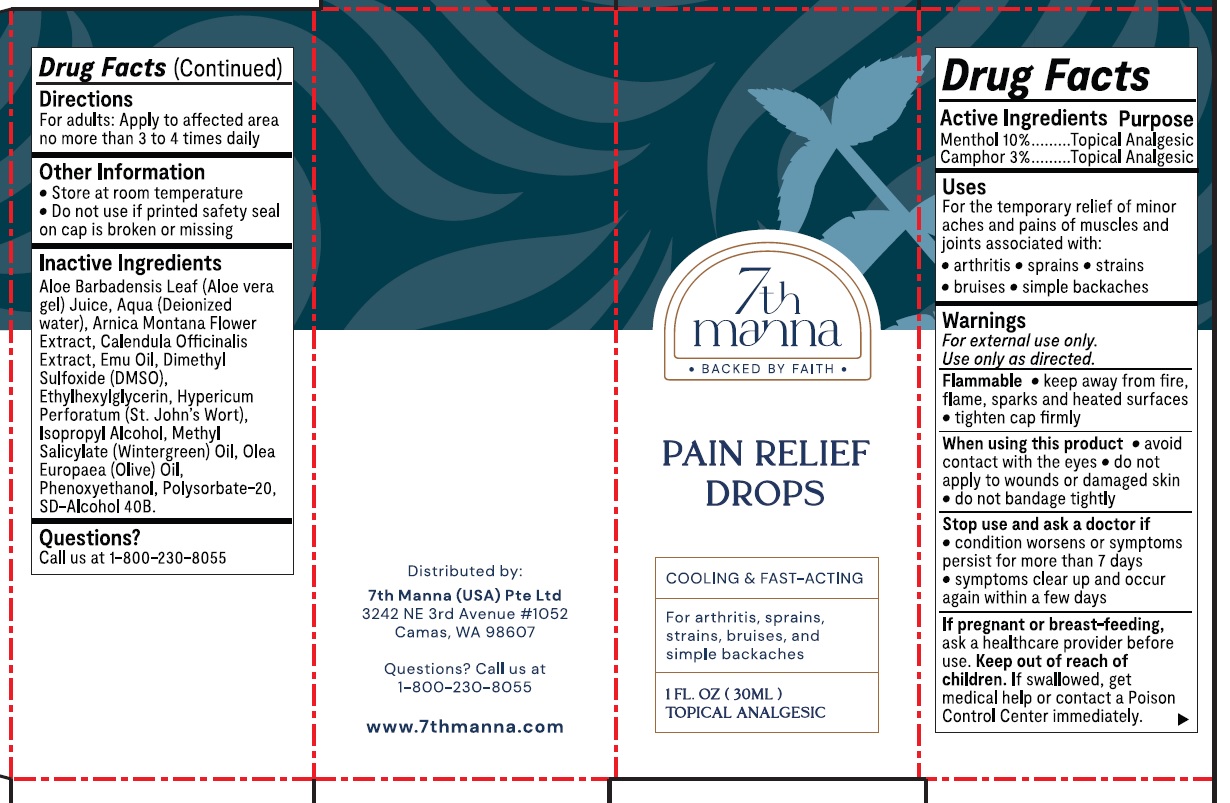 DRUG LABEL: 7th MANNA PAIN RELIEF DROPS
NDC: 71856-423 | Form: LIQUID
Manufacturer: 7TH MANNA (USA) PTE. LTD.
Category: otc | Type: HUMAN OTC DRUG LABEL
Date: 20231111

ACTIVE INGREDIENTS: MENTHOL 100 mg/1 mL; CAMPHOR (SYNTHETIC) 30 mg/1 mL
INACTIVE INGREDIENTS: GREEN OLIVE; PHENOXYETHANOL; POLYSORBATE 20; ALOE VERA LEAF; WATER; ARNICA MONTANA FLOWER; CALENDULA OFFICINALIS FLOWER; EMU OIL; DIMETHYL SULFOXIDE; ETHYLHEXYLGLYCERIN; HYPERICUM PERFORATUM WHOLE; ISOPROPYL ALCOHOL; METHYL SALICYLATE

7th MANNA PAIN RELIEF DROPS

Active Ingredients

Menthol 10%

Camphor 3%

Purpose

Topical Analgesic

Uses

For the temporary relief of minor aches and pains of muscles and joints associated with:

- arthritis
- sprains
- strains
- bruises
- simple backaches

Warnings

For external use only.

Use only as directed.

Flammable

- keep away from fire, flame, sparks and heated surfaces
- tighten cap firmly

When using this product

- avoid contact with the eyes
- do not apply to wounds or damaged skin
- do not bandage tightly

Stop use and ask a doctor if

- condition worsens or symptoms persist for more than 7 days
- symptoms clear up and occur again within a few days

If pregnant or breast-feeding,

ask a healthcare provider before use.

Keep out of reach of children.

If swallowed, get medical help or contact a Poison Control Center immediately.

Directions

For adults: Apply to affected area no more than 3 to 4 times daily

Other Information

- Store at room temperature
- Do not use if printed safety seal on cap is broken or missing

Inactive Ingredients

Aloe Barbadensis Leaf (Aloe vera gel) Juice, Aqua (Deionized water), Arnica Montana Flower Extract, Calendula Officinalis Extract, Emu Oil, Dimethyl Sulfoxide (DMSO),Ethylhexylglycerin, HypericumPerforatum (St.John's Wort),Isopropyl Alcohol, Methyl Salicylate (Wintergreen) Oil, Olea Europaea (Olive) Oil, Phenoxyethanol, Polysorbate-20, SD-Alcohol 40B.

Questions?

Call us at 1-800-230-8055